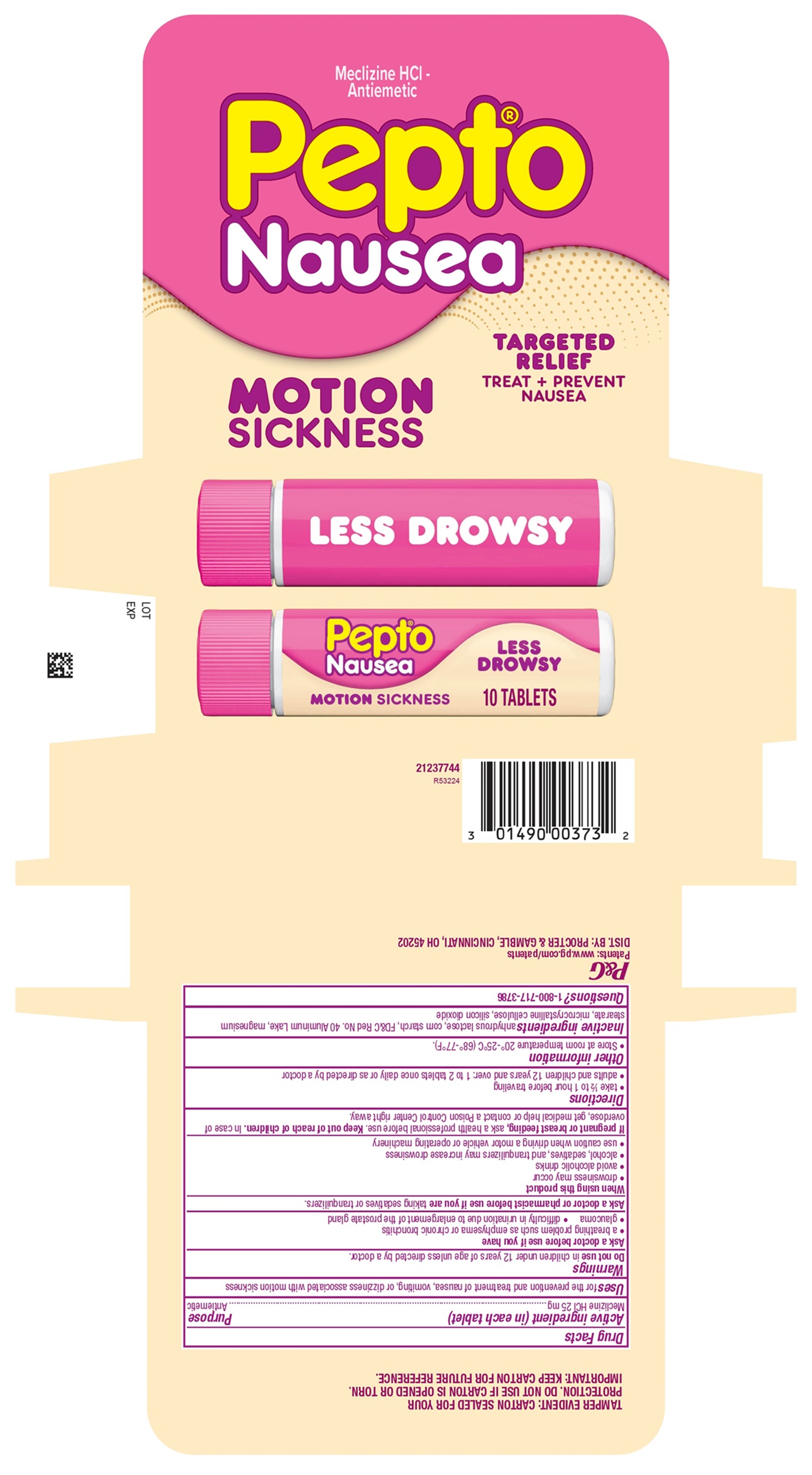 DRUG LABEL: Pepto Nausea
NDC: 84126-340 | Form: TABLET
Manufacturer: THE PROCTER & GAMBLE MANUFACTURING COMPANY
Category: otc | Type: HUMAN OTC DRUG LABEL
Date: 20260218

ACTIVE INGREDIENTS: MECLIZINE HYDROCHLORIDE 25 mg/1 1
INACTIVE INGREDIENTS: ANHYDROUS LACTOSE; STARCH, CORN; FD&C RED NO. 40 ALUMINUM LAKE; MAGNESIUM STEARATE; MICROCRYSTALLINE CELLULOSE; SILICON DIOXIDE

Pepto Nausea MOTION SICKNESS

Pepto Nausea MOTION SICKNESS

Drug Facts

Active ingredient (in each tablet)

Meclizine HCl 25 mg

Purpose

Antiemetic

Uses

for the prevention and treatment of nausea, vomiting, or dizziness associated with motion sickness

Warnings

Do not use

in children under 12 years of age unless directed by a doctor.

Ask a doctor before use if you have

- a breathing problem such as emphysema or chronic bronchitis
- glaucoma
- difficulty in urination due to enlargement of the prostate gland

Ask a doctor or pharmacist before use if you are

taking sedatives or tranquilizers.

When using this product

- drowsiness may occur
- avoid alcoholic drinks
- alcohol, sedatives, and tranquilizers may increase drowsiness
- use caution when driving a motor vehicle or operating machinery

If pregnant or breast feeding,

ask a health professional before use.

OVERDOSAGE

In case of overdose, get medical help or contact a Poison Control Center right away.

Directions

- take ½ to 1 hour before traveling
- adults and children 12 years and over: 1 to 2 tablets once daily or as directed by a doctor

Other information

- Store at room temperature 20°-25°C (68°-77°F).

Inactive ingredients

anhydrous lactose, corn starch, FD&C Red No. 40 Aluminum Lake, magnesium stearate, microcrystalline cellulose, silicon dioxide

Questions?

1-800-717-3786

TAMPER EVIDENT: CARTON SEALED FOR YOUR
PROTECTION. DO NOT USE IF CARTON IS OPENED OR TORN.
IMPORTANT: KEEP CARTON FOR FUTURE REFERENCE.

DIST. BY: PROCTER &

GAMBLE, CINCINNATI, OH

45202

PRINCIPAL DISPLAY PANEL

Meclizine HCl -
Antiemetic

Pepto

Nausea

MOTION

SICKNESS

TARGETED RELIEF

TREAT + PREVENT

NAUSEA

LESS DROWSY

10 TABLETS